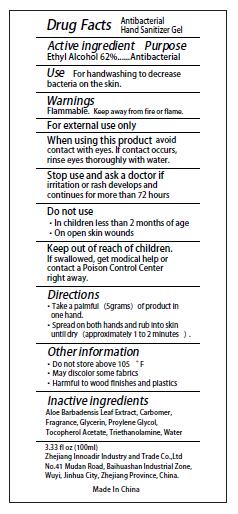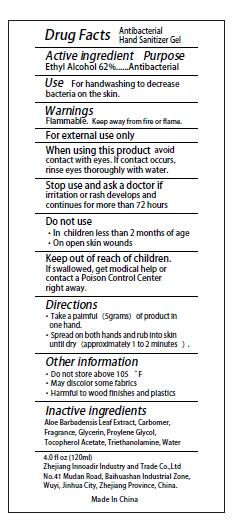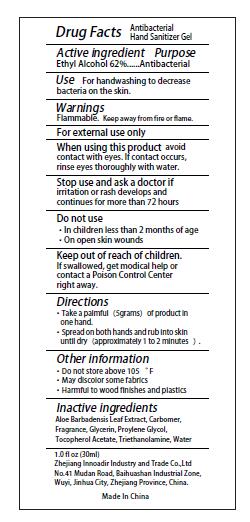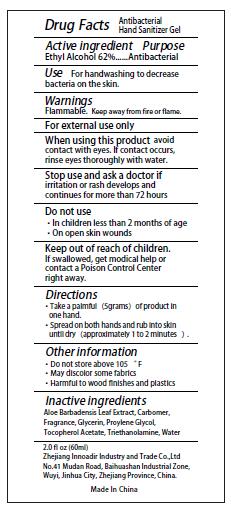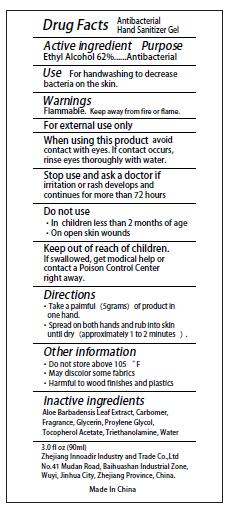 DRUG LABEL: Antibacterial Hand sanitizer
NDC: 76716-006 | Form: GEL
Manufacturer: Zhejiang Innoadir Industry and Trade Co.,Ltd
Category: otc | Type: HUMAN OTC DRUG LABEL
Date: 20200513

ACTIVE INGREDIENTS: ALCOHOL 62 mL/100 mL
INACTIVE INGREDIENTS: TROLAMINE; CARBOMER HOMOPOLYMER TYPE B (ALLYL SUCROSE CROSSLINKED); CHLORHEXIDINE ACETATE; GLYCERIN; ALOE VERA LEAF; WATER; PROPYLENE GLYCOL

Active Ingredient(s)

Ethyl Alcohol 62% v/v. Purpose: Antibacterial

Purpose

Antibacterial

Use

For hand washing to decrease bacteria on the skin

Warnings

Flammable. Keep away from fire or fame

Do not use

- In children less than 2 months of age
- On open sian wounds

When using this product avoidontact with eyes. lf contact occurrinse eyes thoroughly with water.

Stop use and ask a doctor ifimitaton or rash develops andcontinues for more than 72 hours

Keep out of reach of children.If swallowed, get modical help orcontact a Poison Control Center right away.

Directions

- Place enough product on hands to cover all surfaces. Rub hands together until dry.
- Supervise children under 6 years of age when using this product to avoid swallowing.

Other information

- Do not store above 105"F
- May or some rand
- Harmfu to wood finishes and plastics

Inactive ingredients

Aloe Barbadensis Leaf Extract, CarbomerFragrance, Gycein, Prolene Glycol, Tocopherol Acetate,Triethanolamine, Water